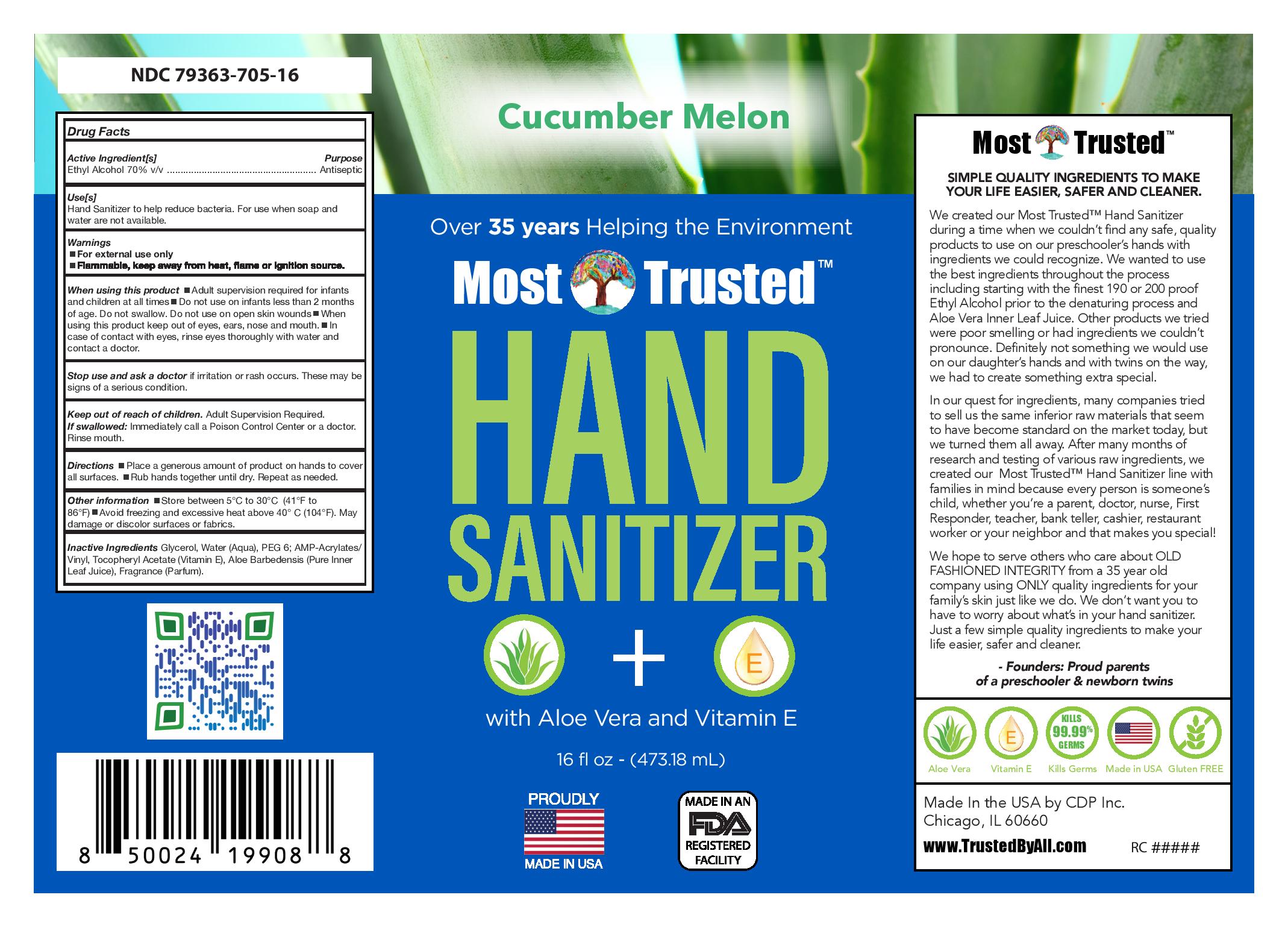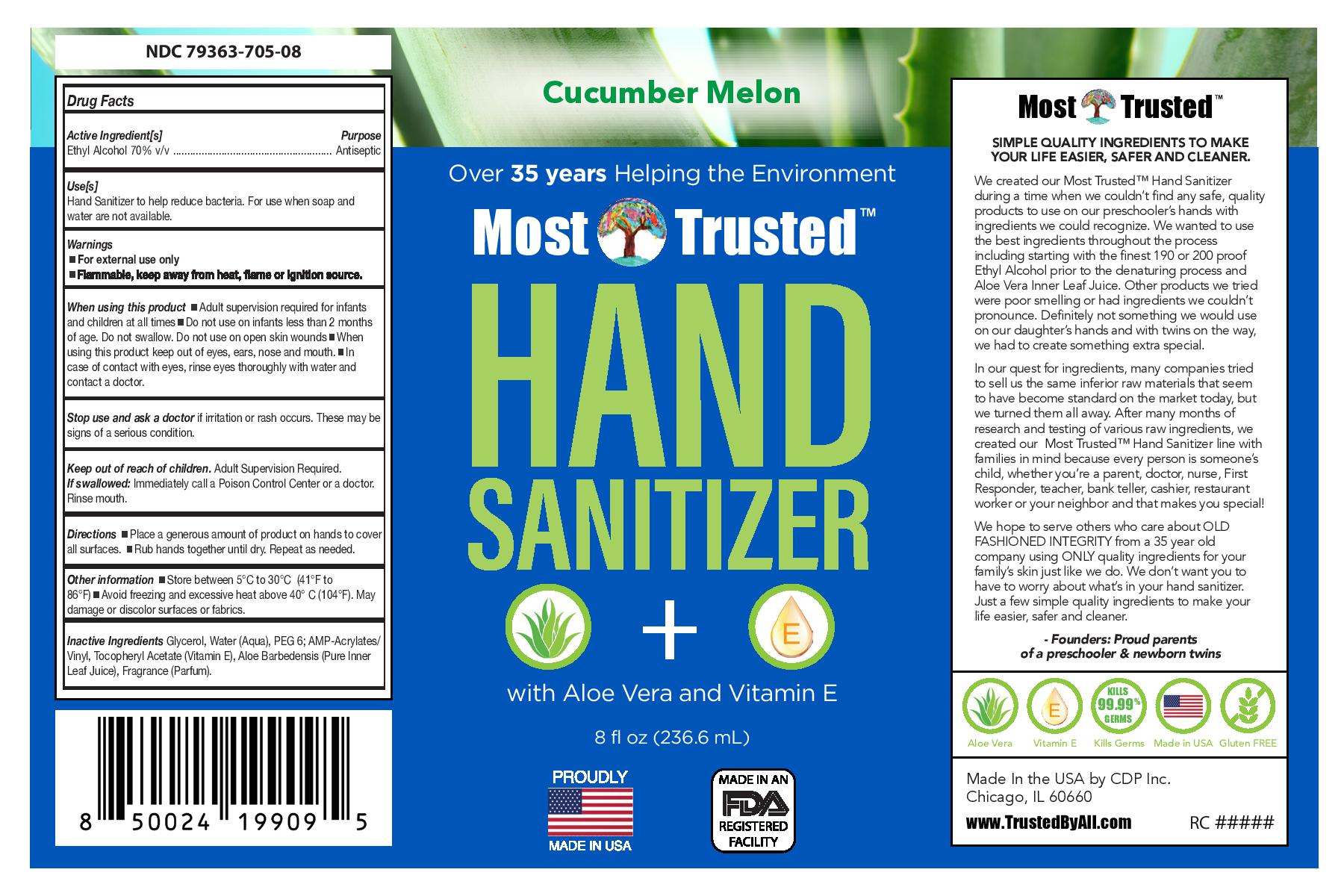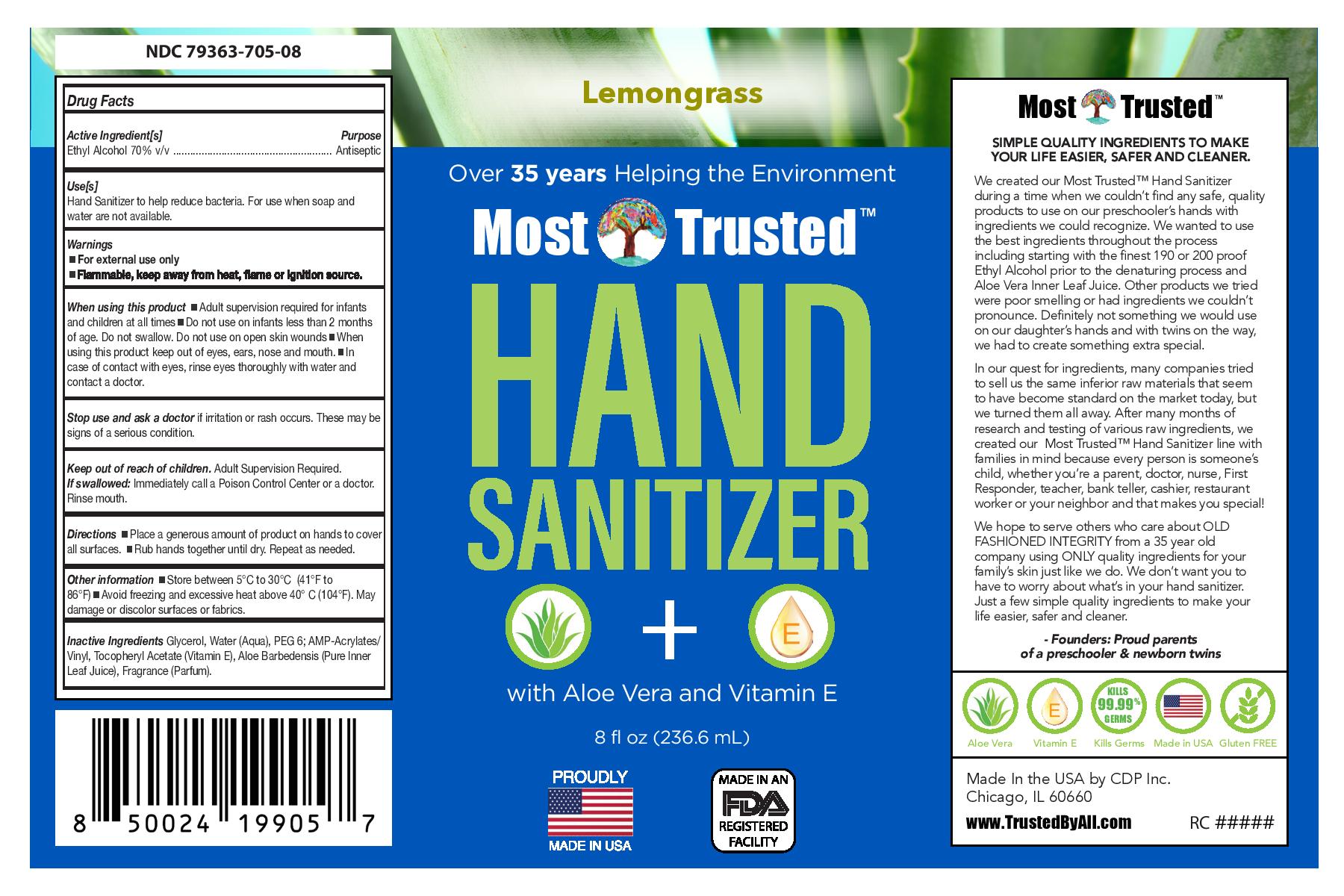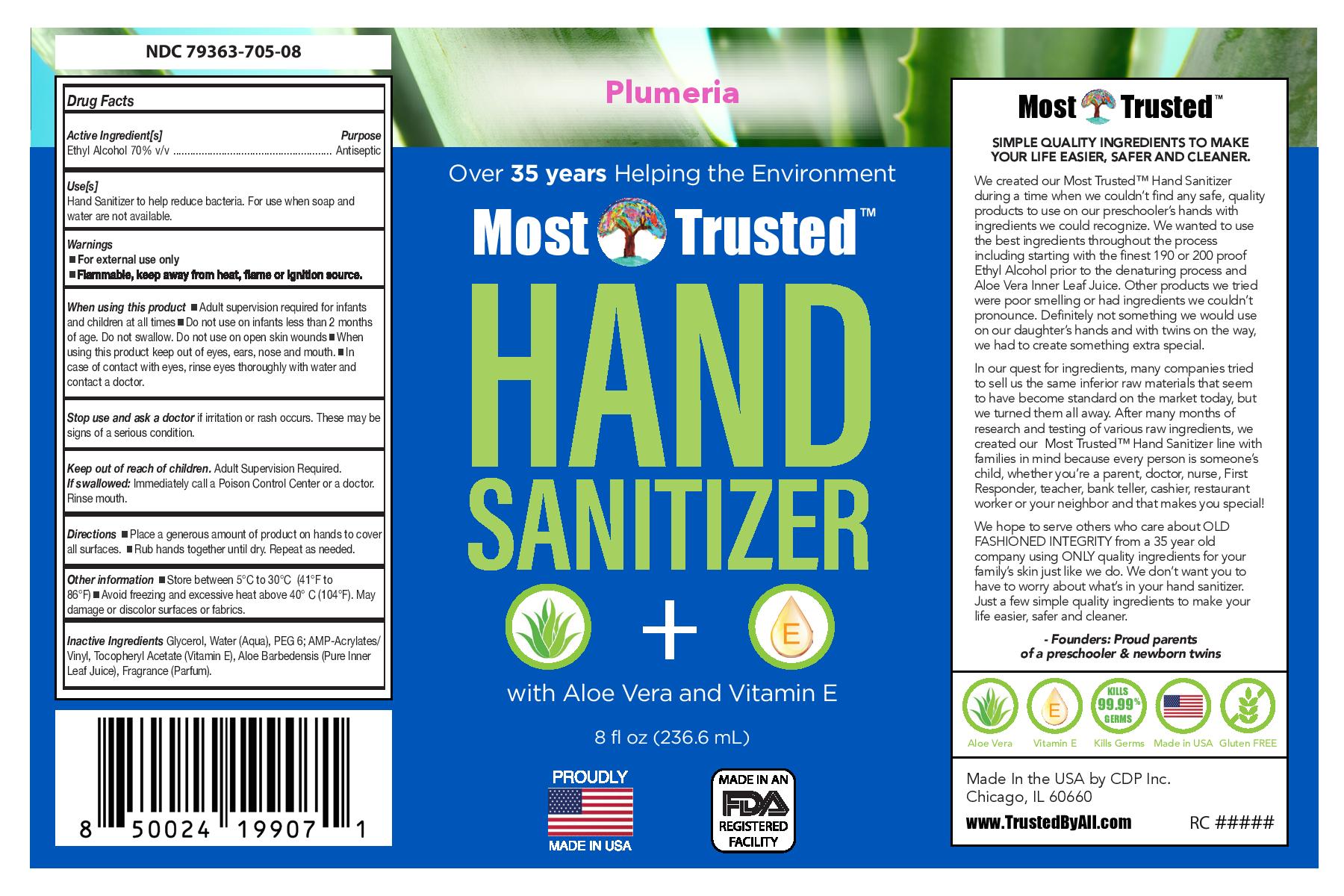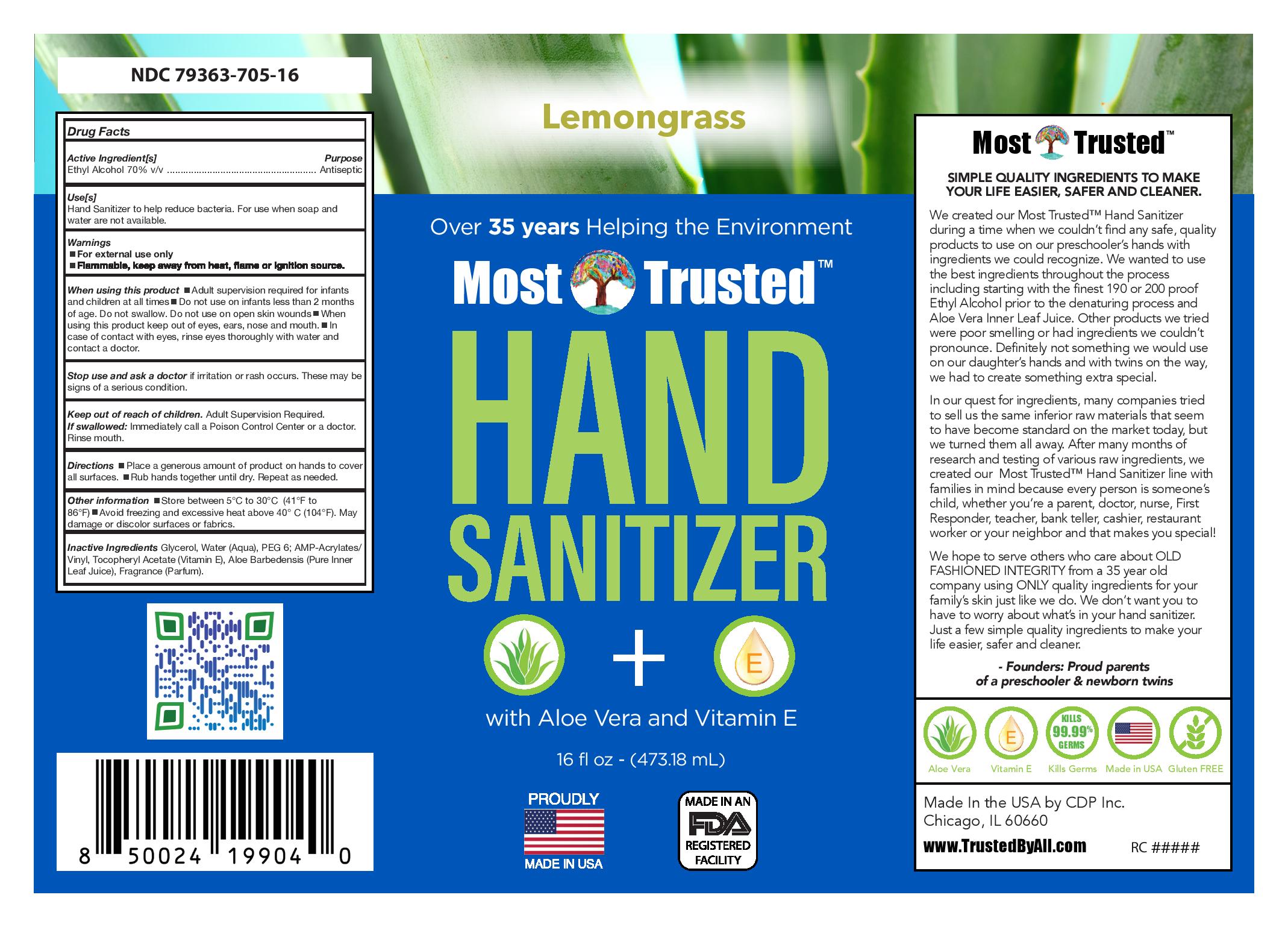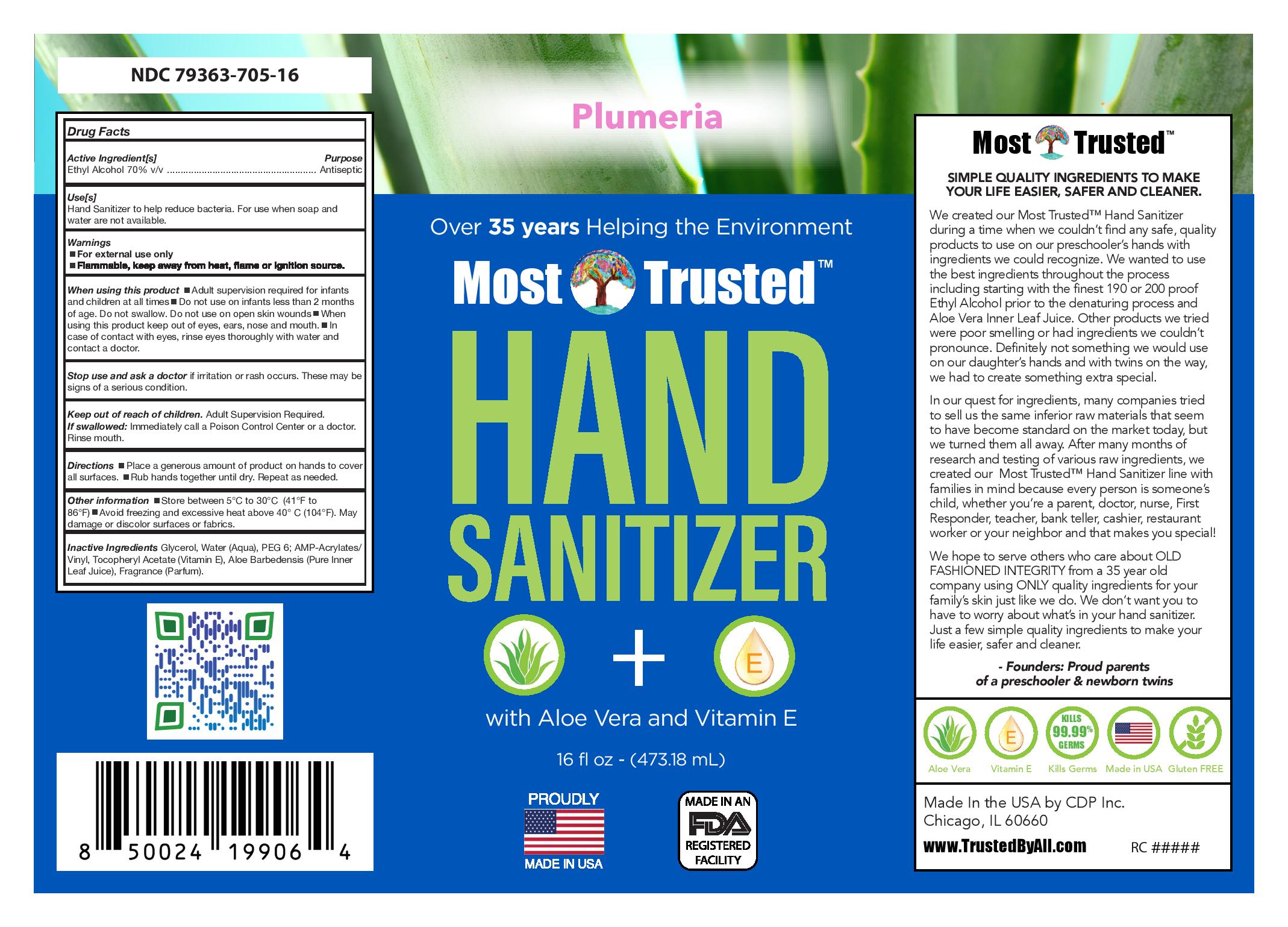 DRUG LABEL: Hand Sanitizer Scented Gel with Aloe and Vit E
NDC: 79363-705 | Form: GEL
Manufacturer: REALCHEM MANUFACTURING
Category: otc | Type: HUMAN OTC DRUG LABEL
Date: 20210125

ACTIVE INGREDIENTS: ALCOHOL 65.7 g/100 g
INACTIVE INGREDIENTS: RAPIDGEL EZ1 1.048 g/100 g; GLYCERIN 2.154 g/100 g; .ALPHA.-TOCOPHEROL ACETATE 0.033 g/100 g; WATER; ALOE VERA LEAF 0.014 g/100 g

70% Gel HS with Vit E/Aloe/Scented

This is a hand sanitizer scented gel containing Vit E and Aloe manufactured according to FDA guidance.

Active Ingredient(s)

Alcohol 70% v/v. Purpose: Antiseptic

Purpose

Antiseptic, Hand Sanitizer

Use

Hand Sanitizer to help reduce bacteria that potentially can cause disease. For use when soap and water are not available.

Warnings

For external use only. Flammable. Keep away from heat or flame

Do not use

- in children less than 2 months of age
- on open skin wounds

When using this product keep out of eyes, ears, and mouth. In case of contact with eyes, rinse eyes thoroughly with water.
Stop use and ask a doctor if irritation or rash occurs. These may be signs of a serious condition.
Keep out of reach of children. If swallowed, get medical help or contact a Poison Control Center right away.

Stop use and ask a doctor if irritation or rash occurs. These may be signs of a serious condition.

Keep out of reach of children. If swallowed, get medical help or contact a Poison Control Center right away.

Directions

- Place enough product on hands to cover all surfaces. Rub hands together until dry.
- Supervise children under 6 years of age when using this product to avoid swallowing.

Other information

- Store between 15-30C (59-86F)
- Avoid freezing and excessive heat above 40C (104F)

Inactive ingredients

glycerin, Rapidgel EZ1, Tocopheryl acetate (Vitanin E), Aloe Barbedensis (Pure Inner Leaf Juice), Fragrance (Parfum), purified water USP

Package Label - Principal Display Panel

237 mL NDC: 79363-705-08

473 ml NDC 79363-705-16